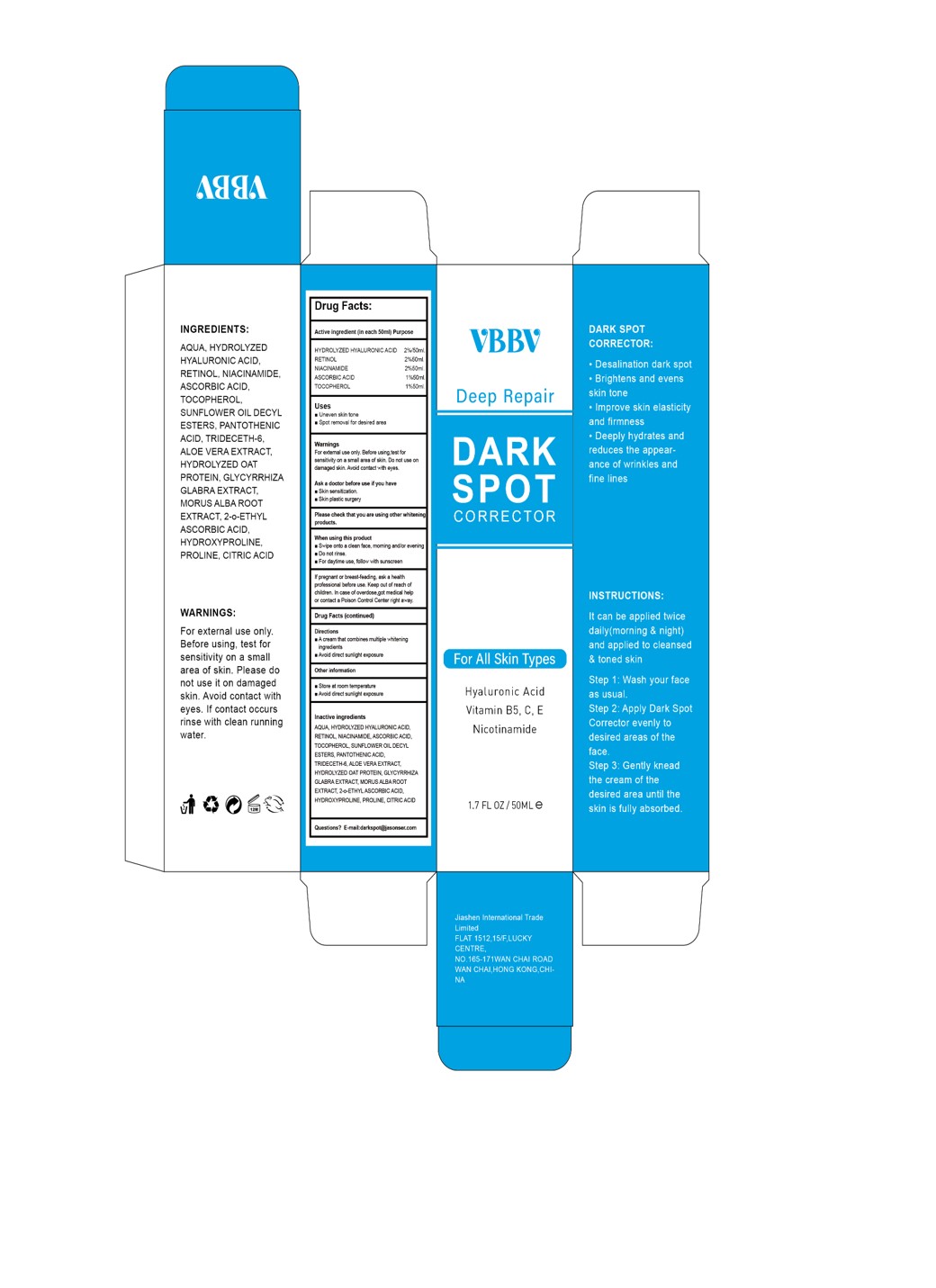 DRUG LABEL: VBBV-DARK SPOT
NDC: 84867-008 | Form: LOTION
Manufacturer: Jiashen International Trading Co., Ltd.
Category: otc | Type: HUMAN OTC DRUG LABEL
Date: 20241120

ACTIVE INGREDIENTS: HYALURONIC ACID 100 mg/50 mL; NIACINAMIDE 100 mg/50 mL; TOCOPHEROL 50 mg/50 mL; ASCORBIC ACID 50 mg/50 mL; RETINOL 100 mg/50 mL
INACTIVE INGREDIENTS: TRIDECETH-6; PANTOTHENIC ACID; GLYCYRRHIZA GLABRA; PROLINE; SUNFLOWER OIL MONO/DIGLYCERIDES; ALOE VERA LEAF; 2-O-ETHYL ASCORBIC ACID; ACONITIC ACID; AVENA SATIVA (OAT) KERNEL EXTRACT; AQUA; MORUS ALBA ROOT; HYDROXYPROLINE

ACTIVE INGREDIENT :

HYDROLYZED HYALURONIC ACID
RETINOL
NIACINAMIDE
ASCORBIC ACID
TOCOPHEROL

INACTIVE INGREDIENT

AQUA
SUNFLOWER OIL DECYL ESTERS
PANTOTHENIC ACID
TRIDECETH-6
ALOE VERA EXTRACT
HYDROLYZED OAT PROTEIN
GLYCYRRHIZA GLABRA EXTRACT
MORUS ALBA ROOT EXTRACT
2-o-ETHYL ASCORBIC ACID
HYDROXYPROLINE
PROLINE
CITRIC ACID

PURPOSE

.Desalination dark spot.Brightens and evensskin tone
.Improve skin elasticityand firmness
.Deeply hydrates andreduces the appear-ance of wrinkles andfine lines

WARNINGS:
For external use only.Before using, test forsensitivity on a smallarea of skin. Please donot use it on damagedskin. Avoid contact witheyes. if contact occursrinse with clean runningwater.

STOP USE

If pregnant or breast-feading, ask a healthprofessional before use. Keep out of reach ofchildren. in case of overdose,got medical helpor contact a Poison Control Center right away.

Ask a doctor before use if you haveSkin sensitization.
Skin plastic surgery

KEEP OUT OF REACH OF CHILDREN

Keep out of reach ofchildren. In case of overdose,got medical helpor contact a Poison Control Center right away.

Uses
neven skin tone
Spot removal for desired area

When using this product
Swipe onto a clean face, moming and'or evening
Do not rinse.
For daytime use, follow with sunscreen

DOSAGE AND ADMINISTRATION

It can be applied twicedaily(morning & night)and applied to cleansed& toned skin
Step 1: Wash your faceas usual.Step 2: Apply Dark SpotCorrector evenly todesired areas of theface.
Step 3: Gently kneadthe cream of thedesired area until theskin is fully absorbed